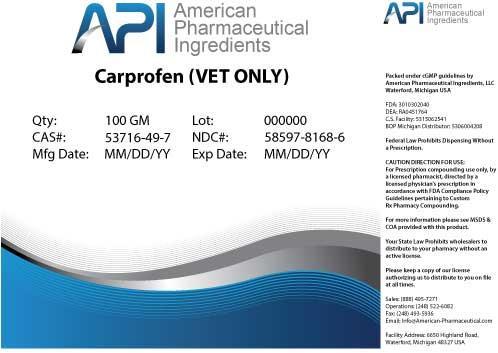 DRUG LABEL: Carprofen
NDC: 58597-8168 | Form: POWDER
Manufacturer: AMERICAN PHARMACEUTICAL INGREDIENTS LLC
Category: other | Type: BULK INGREDIENT
Date: 20140425

ACTIVE INGREDIENTS: Carprofen 1 g/1 g

Carprofen